DRUG LABEL: Trichophyton for Intradermal Skin Testing
NDC: 49643-128 | Form: INJECTION
Manufacturer: Allermed Laboratories, Inc.
Category: prescription | Type: HUMAN PRESCRIPTION DRUG LABEL
Date: 20090513

ACTIVE INGREDIENTS: Trichophyton mentagrophytes 1 g/1000 mL; Trichophyton rubrum 1 g/1000 mL
INACTIVE INGREDIENTS: Sodium chloride 0.25 g/100 mL; Sodium bicarbonate 0.125 g/100 mL; Glycerin 53 mL/100 mL; Phenol 0.4 g/100 mL; Water

ALLERGENIC EXTRACT Trichophyton for Intradermal Skin Testing

WARNINGS

This product is intended for use by physicians who are experienced in the administration of allergenic extracts or for use under the guidance of an allergy specialist. Skin tests should be performed after the patient's physical well being and allergic history have been evaluated. Patients should be instructed to recognize adverse reaction symptoms and cautioned to contact the physician if symptoms occur. As with all allergenic extracts, severe systemic reactions may occur, and in certain individuals these reactions may cause death. Patients should be observed for at least 20 minutes after skin tests have been completed. Emergency measures as well as personnel trained in their use should be immediately available in the event of a life threatening reaction.
This product should never be injected intravenously (see DOSAGE AND ADMINISTRATION). Also, see WARNINGS, PRECAUTIONS, ADVERSE REACTIONS and OVERDOSE Sections below.

DESCRIPTION

Trichophyton extract for diagnostic skin testing is a sterile solution that is prepared by extracting allergenic source material of equal parts of Trichophyton mentagrophytes and Trichophyton rubrum with an aqueous solution of 0.25% sodium chloride, 0.125% sodium bicarbonate and 50% glycerol v/v. Phenol is added at 0.4% w/v as a preservative. Extract for intradermal administration is diluted with the above solution without glycerol.
WEIGHT BY VOLUME (W/V) Weight by volume refers to the weight of raw product added to a measured volume of extraction solution. A 1:500 w/v extract contains 1 gram of source material in 500 mL of solution. The w/v designation refers to concentration rather than potency. Extract labeled w/v has no U.S. Standard of Potency.

CLINICAL PHARMACOLOGY

In sensitive persons, allergenic extract elicits immediate-type skin reactions consisting of erythema and edema at the test site. This allergic inflammatory response is thought to begin with the reaction of allergen with immunoglobulin E (IgE) on the surface of the mast cell. This antigen-antibody reaction initiates a series of biochemical events that result in the release of histamine and other mediators from the mast cell. These mediators are responsible for the characteristic wheal and flare response associated with a positive skin test. The initial antigen-antibody reaction appears to be a specific response that is dependent upon the presence of allergen-specific IgE attached to the mast cell^2,3.
Delayed-type reactions occur in some individuals following the intradermal administration of Trichophyton extract. This response is due to the presence of sensitized lymphocytes. The reaction is characterized by erythema and induration that peaks between 24 and 48 hours after skin testing^4.

INDICATIONS AND USAGE

Intradermal skin tests with Trichophyton extract are indicated for use in persons who are suspected of having Type I hypersensitivity (i.e. allergy) to the fungus.

CONTRAINDICATIONS

Conditions under which the administration of allergenic extract may be contraindicated, depending upon individual circumstances, include: EXTREME SENSITIVITY TO AN ALLERGEN - Determined from the allergic history, or from previous anaphylaxis following skin testing or subcutaneous injection; MYOCARDIAL INFARCTION - Patients who have experienced a recent myocardial infarction may be less able to tolerate the life-threatening effects of a serious adverse reaction. ASTHMA - Patients with highly unstable asthma are at greater risk of fatal reactions from skin tests than are patients without asthma, especially during seasonal exacerbations of the disease. Also, the combination of unstable asthma and treatment with B-adrenergic blockers appears to increase this risk^5. Allergenic extract should be temporarily withheld from patients if any of the following conditions exist: 1) severe symptoms of hay fever and/or asthma; 2) infection or flu accompanied by fever; and 3) exposure to excessive amounts of clinically relevant allergen(s) prior to skin testing.

WARNINGS

Physicians who use allergenic extracts should have a knowledge and practical understanding of allergy skin testing as described in the published literature^6,7,8.
Allergenic extracts are manufactured to assure high potency and therefore have the ability to cause serious local and systemic reactions, including death in highly sensitive patients^5. Patients should be informed of the risks of skin testing and instructed in the recognition of symptoms of an adverse allergic reaction (see PRECAUTIONS and ADVERSE REACTIONS below).
Excessively large local reactions or systemic reactions are more likely to occur if the patient is skin tested shortly after exposure to allergens to which he or she is sensitive.

PRECAUTIONS

GENERAL It is recommended that the device used to perform skin tests be disposable to prevent the possibility of accidental transfer of serum hepatitis, HIV and other infectious agents from one person to another. Injectable epinephrine should be available when skin tests are administered (see ADVERSE REACTIONS).
PATIENT INFORMATION Skin tests with allergenic extracts are usually safe and effective in the diagnosis of allergic diseases when used properly and when interpreted in conjunction with the allergic history and clinical findings. Patients should be observed in the office for 20 minutes after skin tests have been completed^9 and instructed to return to the office or emergency room if symptoms of an allergic reaction or shock occur. The risk of a serious adverse reaction is always present. However, it is minimized by the use of the prick-puncture procedure as the initial method of testing. In a study of 16,204 persons in the United States between 6 and 74 years of age, no anaphylactic reactions were observed after prick-puncture skin testing with eight different allergenic extracts. The authors concluded that the risk of adverse reactions to prick-puncture skin tests is low and similar to other routine medical procedures, such as venipuncture^10.
Since drugs may affect the reactivity of the skin, patients should be instructed to avoid medications, particularly antihistamines and sympathomimetic drugs prior to skin testing (see DRUG INTERACTION below).
DRUG INTERACTION Treatment with beta-blocking drugs may make patients refractory to the usual dose of epinephrine, in the event epinephrine is required to control an adverse reaction^11.
Since drugs may affect the reactivity of the skin, patients should be instructed to avoid medications, particularly antihistamines and sympathomimetic drugs for at least 24 hours prior to skin testing. Non-sedating antihistamine suppresses the erythema/edema response for longer periods and should be withheld according to information included in the package insert. Adrenal corticosteroids and ACTH do not alter the immediate hypersensitivity reaction of the skin but do reduce delayed-type reactions associated with cellular hypersensitivity.
CARCINOGENESIS, MUTAGENESIS, IMPAIRMENT OF FERTILITY Long-term studies in animals have not been conducted with allergenic extracts to determine their potential for carcinogenicity, mutagenicity or impairment of fertility.
PREGNANCY CATEGORY C Allergenic Extracts. Animal reproduction studies have not been conducted with allergenic extracts. It is also not known whether allergenic extracts can cause fetal harm when administered to a pregnant woman or can affect reproduction capacity. Allergenic extracts should be given to a pregnant woman only if clearly needed. Since studies indicate no increased risk to the fetus or to the mother who is treated cautiously with immunotherapy during a normal pregnancy, it is unlikely that extract administered by skin test will be harmful. However, on the basis of histamine's known ability to contract uterine muscle, extensive testing with its possibility of histamine release should be avoided during pregnancy. Also, immunologic suppressive action can occur during pregnancy and for this reason it is possible that the results of allergy skin tests may not accurately reflect the allergic state of the pregnant patient^12.
NURSING MOTHERS It is not known whether this drug is excreted in human milk. Because many drugs are excreted in human milk, caution should be exercised when allergenic extract is administered to a nursing woman.
PEDIATRIC USE The procedures and precautions that are observed in skin testing adults should be observed with children^13.

ADVERSE REACTIONS

LOCAL REACTIONS Large, persistent local reactions or minor exacerbations of the patient's allergic symptoms may be treated by local cold applications and/or the use of oral anti-histamines.
SYSTEMIC REACTIONS Allergenic extracts are highly potent and in highly sensitive individuals can cause systemic symptoms, including anaphylaxis. It cannot be overemphasized that anaphylactic shock is always a possibility under certain unpredictable combinations of circumstances. Other possible systemic reaction symptoms may include fainting, pallor, bradycardia, hypotension, angioedema, cough, wheezing, conjunctivitis, rhinitis and urticaria. Therefore, it is imperative that physicians administering skin tests understand and be prepared to treat severe allergic reactions.
If a systemic or anaphylactic reaction occurs during or following skin testing, the patient should be treated with 1:1000 epinephrine hydrochloride. The recommended dose: infants to 2 years of age 0.05 to 0.1 mL, children 2 to 6 years, 0.15 mL, children 6 to 12 years, 0.2 mL, adults 0.3 - 0.5 mL. If necessary, treatment may be repeated up to three times every 10 - 15 minutes.
After administration of epinephrine, profound shock or vasomotor collapse should be treated with intravenous fluids and possibly vasoactive drugs. Oxygen should be given by mask. Intravenous antihistamine, aminophylline, inhaled bronchodilators or adrenal corticosteroids may be used if necessary after adequate epinephrine and circulatory support have been given. Emergency resuscitation measures and personnel trained in their use should be available immediately. The physician should be prepared in advance for all contingencies. Promptness in beginning emergency treatment is of utmost importance^14.
Serious adverse reactions should be reported to MedWatch: The FDA Safety Information and Adverse Event Reporting Program, Office Of The Center Director, Center for Drug Evaluation and Research, 5515 Security Lane, Suite 5100, Rockville, MD 20852, Telephone (800) 332-1088.

OVERDOSAGE

The signs and symptoms of overdosage are the same as those listed under ADVERSE REACTIONS, paragraphs 1 and 2.
The treatment of a systemic allergic reaction resulting from skin tests should include the following:

- The patient should be placed in the recumbent position to maintain blood flow to the head.
- Aqueous epinephrine 1:1,000 should be administered subcutaneously. See ADVERSE REACTIONS for dose and other supportive measures.
- Reassurance should be provided.

The above steps should be performed nearly simultaneously and as soon as possible after the reaction begins. Persistent wheezing may necessitate treatment with intravenous aminophylline and inhaled bronchodilators. For profound shock and hypotension, intravenous fluids, vasopressors and oxygen also may be needed. Maintenance of an open airway is critical if upper airway obstruction is present. Corticosteroids may provide benefit if symptoms are prolonged or recurrent.

DOSAGE AND ADMINISTRATION

Prior to administering skin tests, the skin should be cleaned with alcohol and allowed to dry completely. The tests should be placed on the volar surface of the forearm and four rows may be placed on the back.
INTRADERMAL TEST The intradermal test is performed by administering 0.1 mL of extract into the skin. The injection should be given as superficially as possible creating a distinct bleb approximately 5 mm in diameter. The tests should be examined after 15 - 20 minutes and read as negative or positive. Test sites that show a wheal and flare response should be measured and reported in mm of edema and erythema or scored as 1+ to 4+ based on a mm reference scale. Induration after 24 - 48 hours can occur in some individuals and also may be recorded in mm.

HOW SUPPLIED

One mL of extract for intradermal skin testing is supplied in 2 mL sealed multidose vials. Each vial contains enough extract for 10 tests.

STORAGE

Extract should be stored at 2°C to 8°C, since higher temperatures may adversely affect the stability of allergens. Do not freeze.

REFERENCES

1. Turkeltaub, P.C., The allergy unit - clinical relevance: Issues in allergen standardization, In: Lockey, R.F., S.C. Bukantz (Eds), Allergen Immunotherapy, Marcel Dekkar, New York, 171, 1991.
2. Ting, S., E.H. Dunsky, R.M. Lavker, et al., Patterns of mast cell alterations and in vivo mediator release in human allergic skin reactions, J. Allergy Clin. Immunol., 66:417, 1980.
3. Zweiman, B., Mediators of allergic inflammation in the skin, Clin. Allergy, 18:419, 1988.
4. Askenase, Philip W., Effector and regulatory mechanisms in delayed-type hypersensitivity, Allergy Principles and Practice, vol.1, p. 264, third edition, C.V. Mosby, St. Louis, 1988.
5. Lockey, R.F., L.M. Benedict, P.C. Turkeltaub, S.C. Buicantz, Fatalities from immunotherapy (IT) and skin testing (ST), J. Allergy and Clinical Immunol., 79:660, 1987.
6. Nelson, H.S., Diagnostic procedures in allergy: I. Allergy skin testing, Ann. Allergy, 51: 411, 1983.
7. Bierman, C.W., D.S. Pearlman, G.G. Shapiro, W.W. Busse (Eds), Allergic disease from infancy to adulthood, Third edition, W.B. Saunders Co., Philadelphia, 1996.
8. Middleton, E., Jr., C.E. Reed, E.F. Ellis, N.F. Adkinson, J.W. Yunginger (Eds), Allergy principles and practice, Fourth edition, C.V. Mosby, St. Louis, 1993.
9. Executive Committee, The American Academy of Allergy and Clinical Immunology, Position Statement, The waiting period after allergen skin testing and immunotherapy, J. Allergy Clin. Immunol., 85:526, 1990.
10. Turkeltaub, P.C., P.J. Gergen, The risk of adverse reactions from percutaneous prick-puncture allergen skin testing, venipuncture and body measurements: data from the second National Health and Nutrition Examination Survey (NHANES II) 1976-1980, J. Allergy Clin. Immunol., 84:886, 1989.
11. Jacobs, Robert L., Goeffrey W. Rake, Jr., et al., Potentiated anaphylaxis in patients with drug-induced beta-adrenergic blockade, J. Allergy and Clinical Immunol., 68:125, 1981.
12. Weinstein, A.M., D.B. Dubin, W. K. Podleski, L.L. Spector, R.S. Farr, Asthma and pregnancy, JAMA 134: 1161, 1979.
13. Sly, M.R., Pediatric allergy, Medical Examination Publishing Co., Inc., Second edition, p.352, 1981.
14. Executive Committee, The American Academy of Allergy and Clinical Immunology, Position Statement, Personnel and equipment to treat systemic reactions caused by immunotherapy with allergenic extracts. J. Allergy and Clinical Immunol., 77:271, 1986.